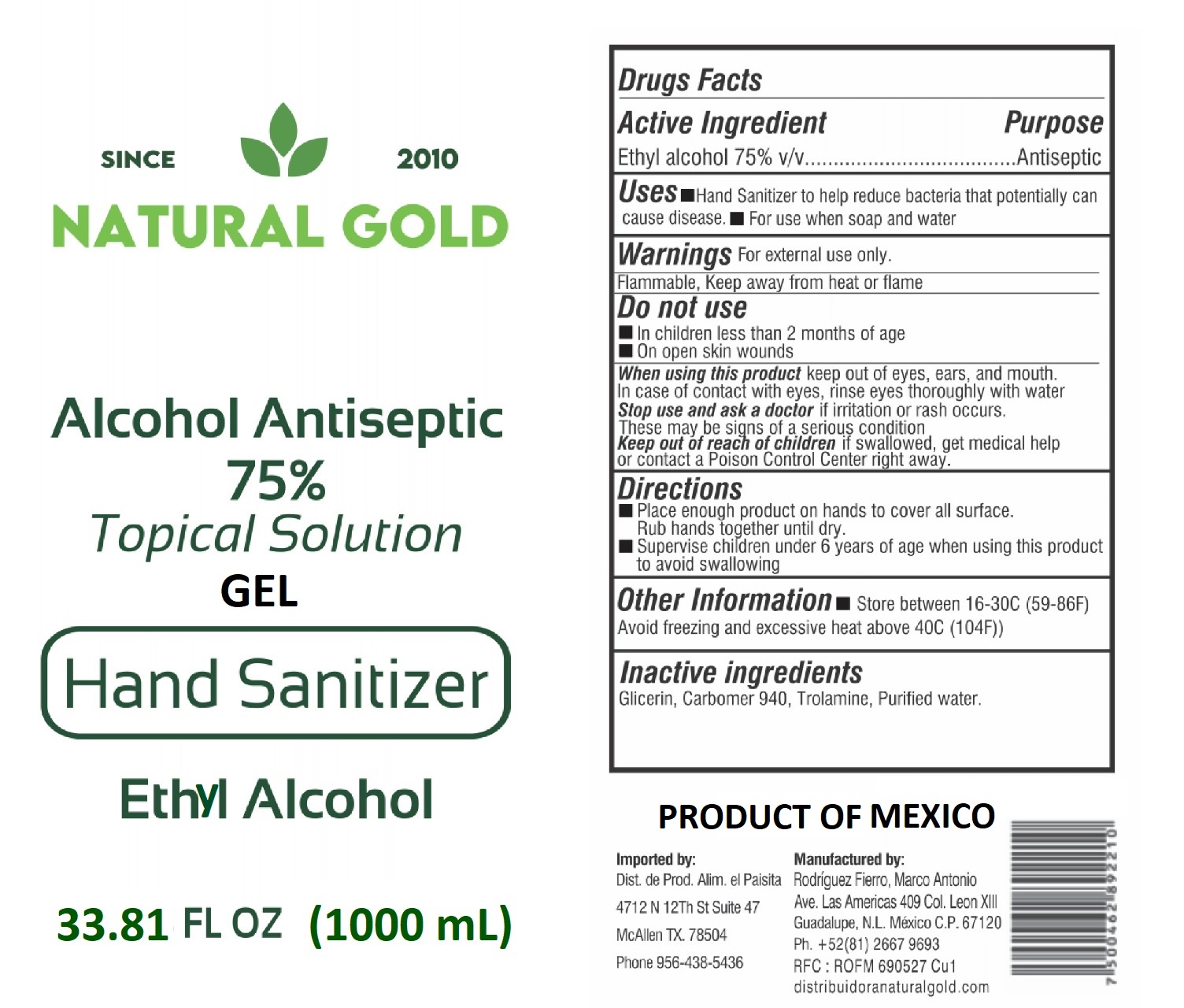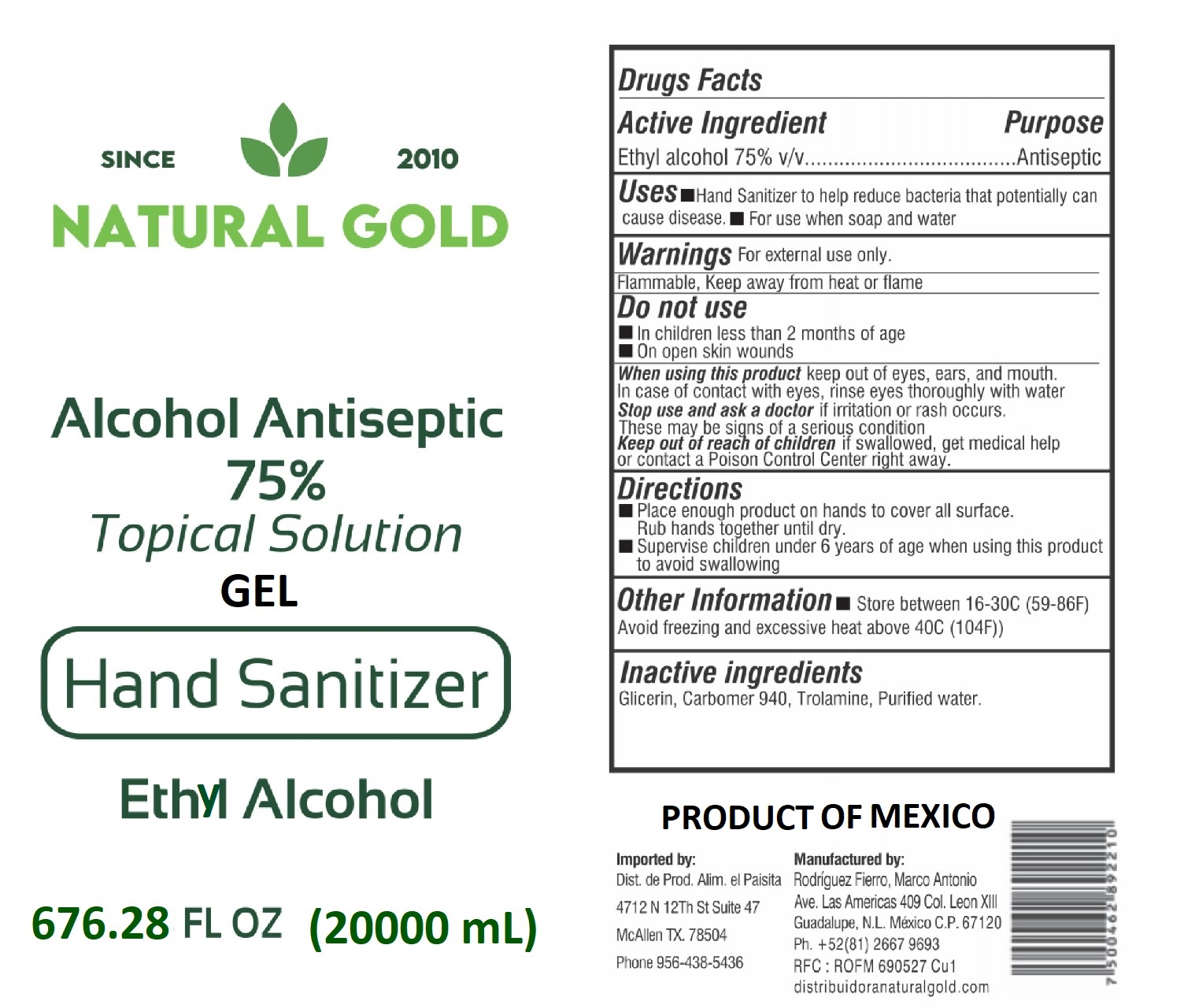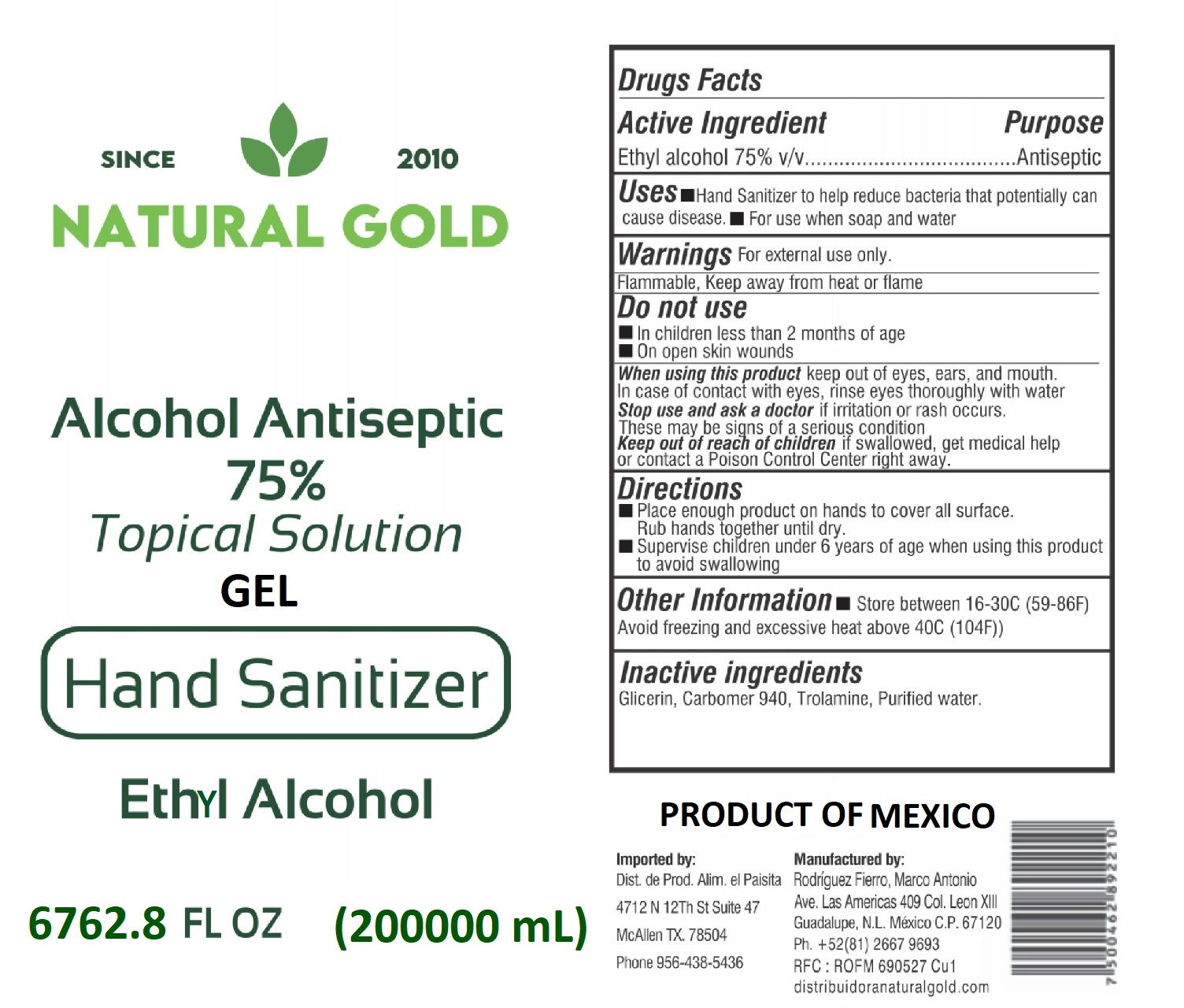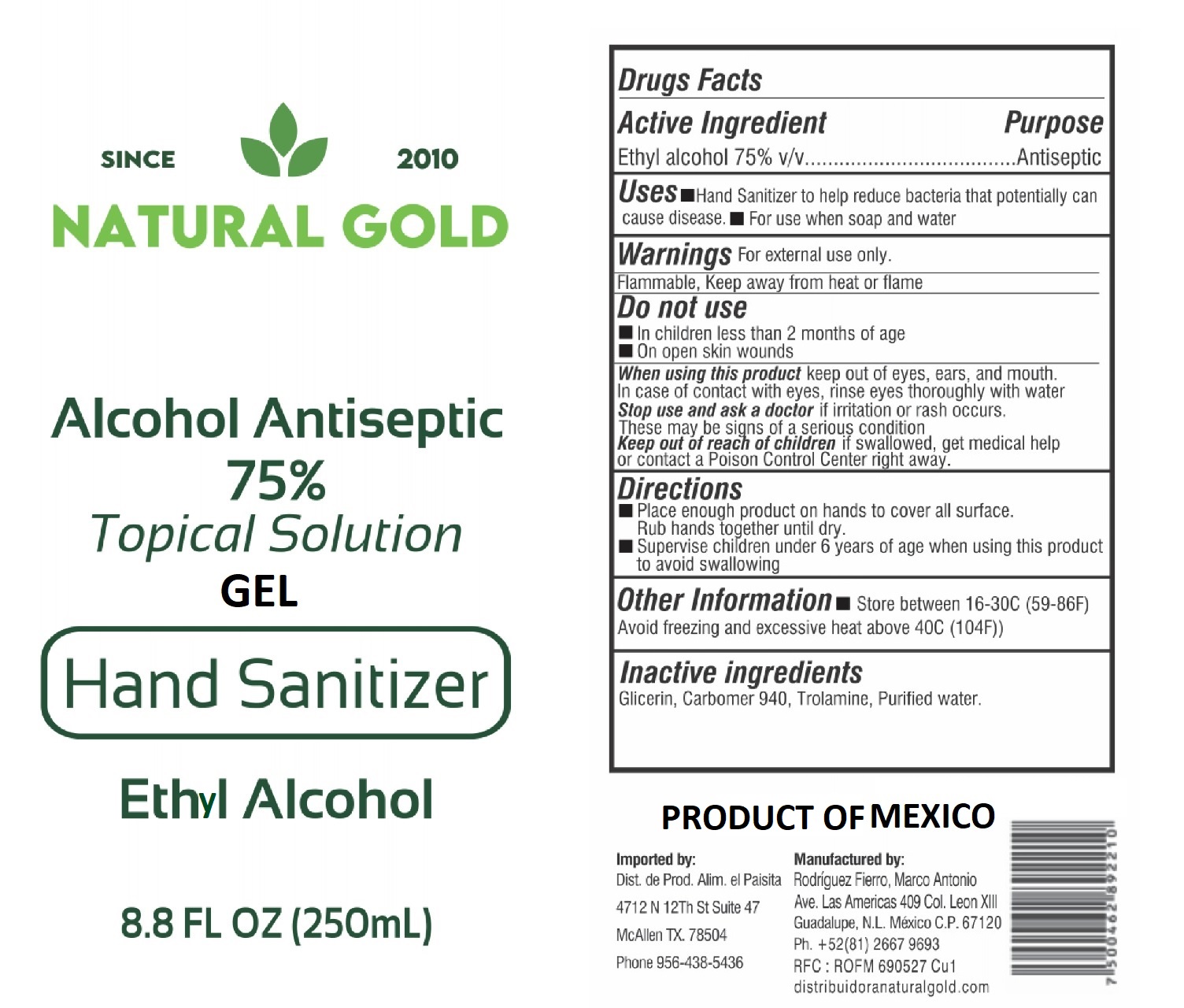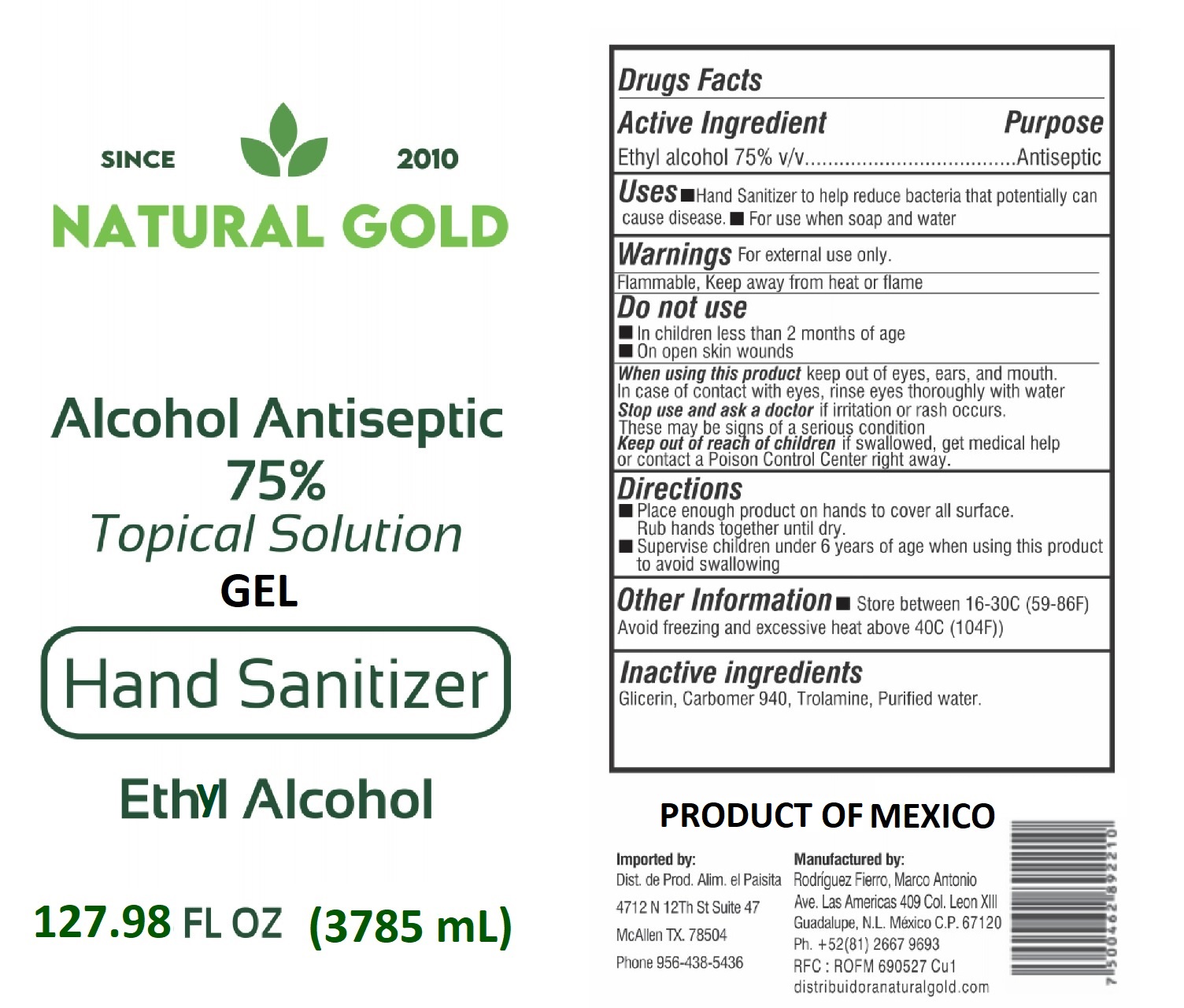 DRUG LABEL: Hand Sanitizer
NDC: 78368-577 | Form: GEL
Manufacturer: Rodríguez Fierro, Marco Antonio
Category: otc | Type: HUMAN OTC DRUG LABEL
Date: 20200608

ACTIVE INGREDIENTS: ALCOHOL 75 mL/100 mL
INACTIVE INGREDIENTS: CARBOMER 940 0.75 mL/100 mL; GLYCERIN 1.45 mL/100 mL; TROLAMINE 0.25 mL/100 mL; WATER

Hand Sanitizer

Active Ingredient(s)

Alcohol 75% v/v. Purpose: Antiseptic

Purpose

Antiseptic, Hand Sanitizer

Use

Hand Sanitizer to help reduce bacteria that potentially can cause disease. For use when soap and water are not available.

Warnings

For external use only. Flammable. Keep away from heat or flame

Do not use

- in children less than 2 months of age
- on open skin wounds

When using this product keep out of eyes, ears, and mouth. In case of contact with eyes, rinse eyes thoroughly with water.
Stop use and ask a doctor if irritation or rash occurs. These may be signs of a serious condition.
Keep out of reach of children. If swallowed, get medical help or contact a Poison Control Center right away.

Stop use and ask a doctor if irritation or rash occurs. These may be signs of a serious condition.

Keep out of reach of children. If swallowed, get medical help or contact a Poison Control Center right away.

Directions

- Place enough product on hands to cover all surfaces. Rub hands together until dry.
- Supervise children under 6 years of age when using this product to avoid swallowing.

Other information

- Store between 15-30C (59-86F)
- Avoid freezing and excessive heat above 40C (104F)

Inactive ingredients

glycerin, carbomer 940, trolamine, purified water

Package Label - Principal Display Panel

250 mL NDC: 78368-577-17

Package Label - Principal Display Panel

1000 mL NDC: 78368-577-18

Package Label - Principal Display Panel

3785 mL NDC: 78368-577-19

Package Label - Principal Display Panel

20000 mL NDC: 78368-577-20

Package Label - Principal Display Panel

200000 mL NDC: 78368-577-21